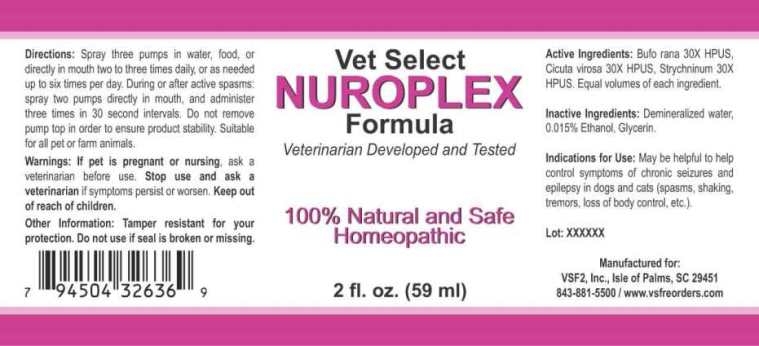 DRUG LABEL: Nuroplex
NDC: 86100-0010 | Form: LIQUID
Manufacturer: Vsf2, Inc.
Category: homeopathic | Type: OTC ANIMAL DRUG LABEL
Date: 20251110

ACTIVE INGREDIENTS: BUFO BUFO CUTANEOUS GLAND 30 [hp_X]/1 mL; CICUTA VIROSA ROOT 30 [hp_X]/1 mL; STRYCHNINE 30 [hp_X]/1 mL
INACTIVE INGREDIENTS: WATER; ALCOHOL; GLYCERIN

Drug Facts:

ACTIVE INGREDIENTS:

Bufo rana 30X HPUS, Cicuta virosa 30X HPUS, Strychninum 30X HPUS, Equal volumes of each ingredient.

INDICATIONS FOR USE:

May be helpful to help control symptoms of chronic seizures and epilepsy in dogs and cats (spasms, shaking, tremors, loss of body control, etc.).

WARNINGS:

If pet is pregnant or nursing, ask a veterinarian before use.

Stop use and ask a veterinarian if symptoms persist or worsen.

Keep out of reach of children.

Other Information: Tamper resistant for your protection. Do not use if seal is broken or missing.

KEEP OUT OF THE REACH OF CHILDREN:

Keep out of reach of children.

DIRECTIONS:

Spray three pumps in water, food or directly in mouth two to three times daily, or as needed up to six times per day. During or after active spasms: spray two pumps directly in mouth, and administer three times in 30 second intervals. Do not remove pump top in order to ensure product stability. Suitable for all pet or farm animals.

INDICATIONS FOR USE:

May be helpful to help control symptoms of chronic seizures and epilepsy in dogs and cats (spasms, shaking, tremors, loss of body control, etc.).

INACTIVE INGREDIENTS:

Demineralized water, 0.015% Ethanol, Glycerin.

QUESTIONS:

Manufactured for:

VSF2, Inc., Isle of Palms, SC 29451

843-881-5500 / www.vsfreorders.com

PACKAGE LABEL DISPLAY:

Vet Select

NUROPLEX

Formula

Veterinarian Developed and Tested

100% Natural and Safe

Homeopathic

2 fl. oz. (59 ml)